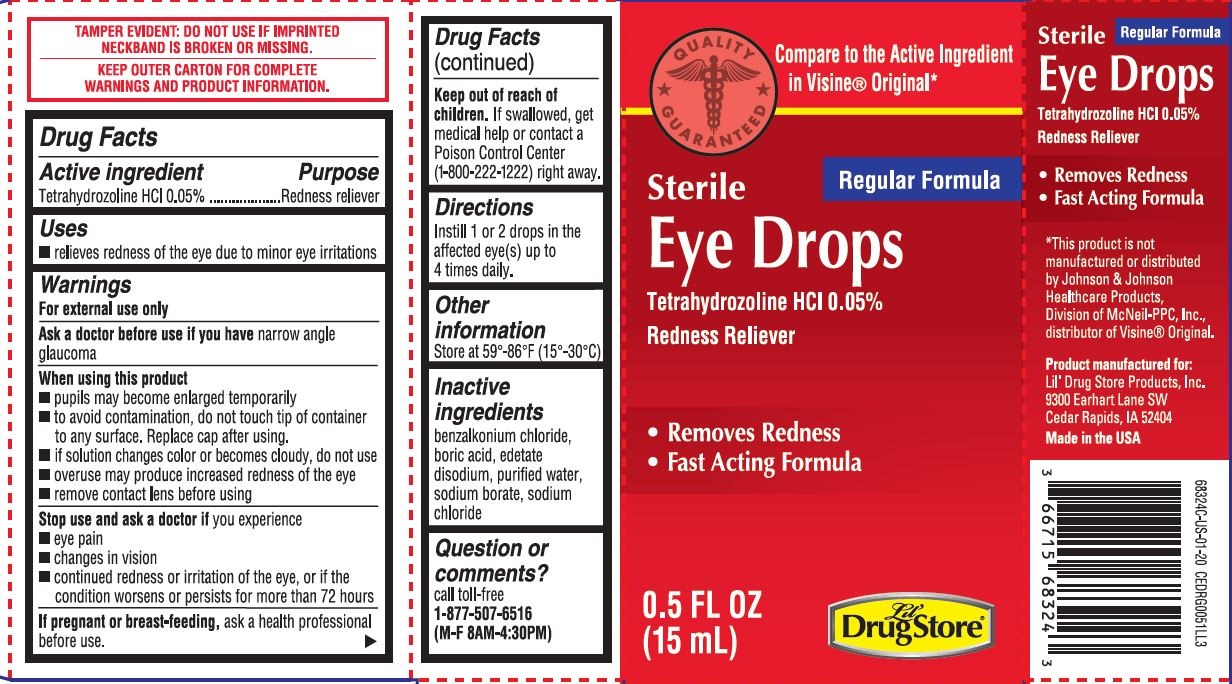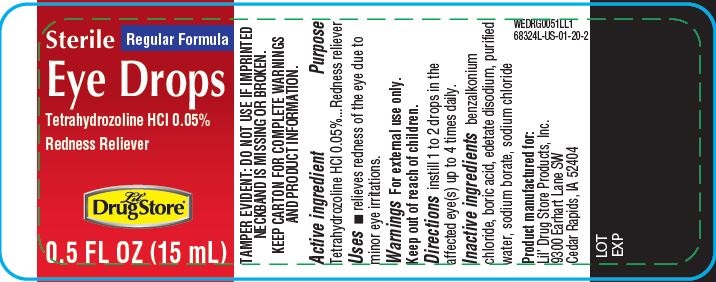 DRUG LABEL: Lil Drug Store Eye Drops
NDC: 66715-6832 | Form: LIQUID
Manufacturer: Lil Drug Store Products, Inc
Category: otc | Type: HUMAN OTC DRUG LABEL
Date: 20241230

ACTIVE INGREDIENTS: TETRAHYDROZOLINE HYDROCHLORIDE 0.5 mg/1 mL
INACTIVE INGREDIENTS: BENZALKONIUM CHLORIDE; BORIC ACID; EDETATE DISODIUM; WATER; SODIUM BORATE; SODIUM CHLORIDE

Lil' Drug Store® Eye Drops
Redness Reliever

Drug Facts

Active ingredient

Tetrahydrozoline HCl 0.05%

Purpose

Redness reliever

Uses

- relieves redness of the eye due to minor eye irritations

Warnings

For external use only

Ask a doctor before use if you have narrow angle glaucoma

When using this product

- pupils may become enlarged temporarily
- to avoid contamination, do not touch tip of container to any surface. Replace cap after using.
- if solution changes color or becomes cloudy, do not use
- overuse may produce increased redness of the eye
- remove contact lens before using

Stop use and ask a doctor if you experience

- eye pain
- changes in vision
- continued redness or irritation of the eye, or if the condition worsens or persists for more than 72 hours

PREGNANCY OR BREAST FEEDING

If pregnant or breast-feeding, ask a health professional before use.

Keep out of reach of children. If swallowed, get medical help or contact a Poison Control Center (1-800-222-1222) right away.

Directions

Instill 1 or 2 drops in the affected eye(s) up to four times daily.

Other information

Store at 59°-86°F (15°-30°C)

Inactive ingredients

benzalkonium chloride, boric acid, edetate disodium, purified water, sodium borate, sodium chloride

Question or comments?

call toll-free 1-877-507-6516 (M-F 8AM-4:30PM)

Product distributed by:
Lil' Drug Store Products, Inc.
1201 Continental Place NE
Cedar Rapids, IA 52402

PRINCIPAL DISPLAY PANEL - 15 mL Bottle Carton

QUALITY
GUARANTEED

Compare to the Active Ingredient
in Visine® Original*

Regular Formula

Sterile
Eye Drops

Tetrahydrozoline HCl 0.05%
Redness Reliever

- Removes Redness
- Fast Acting Formula

0.5 FL OZ
(15 mL)

Lil'
Drug Store®